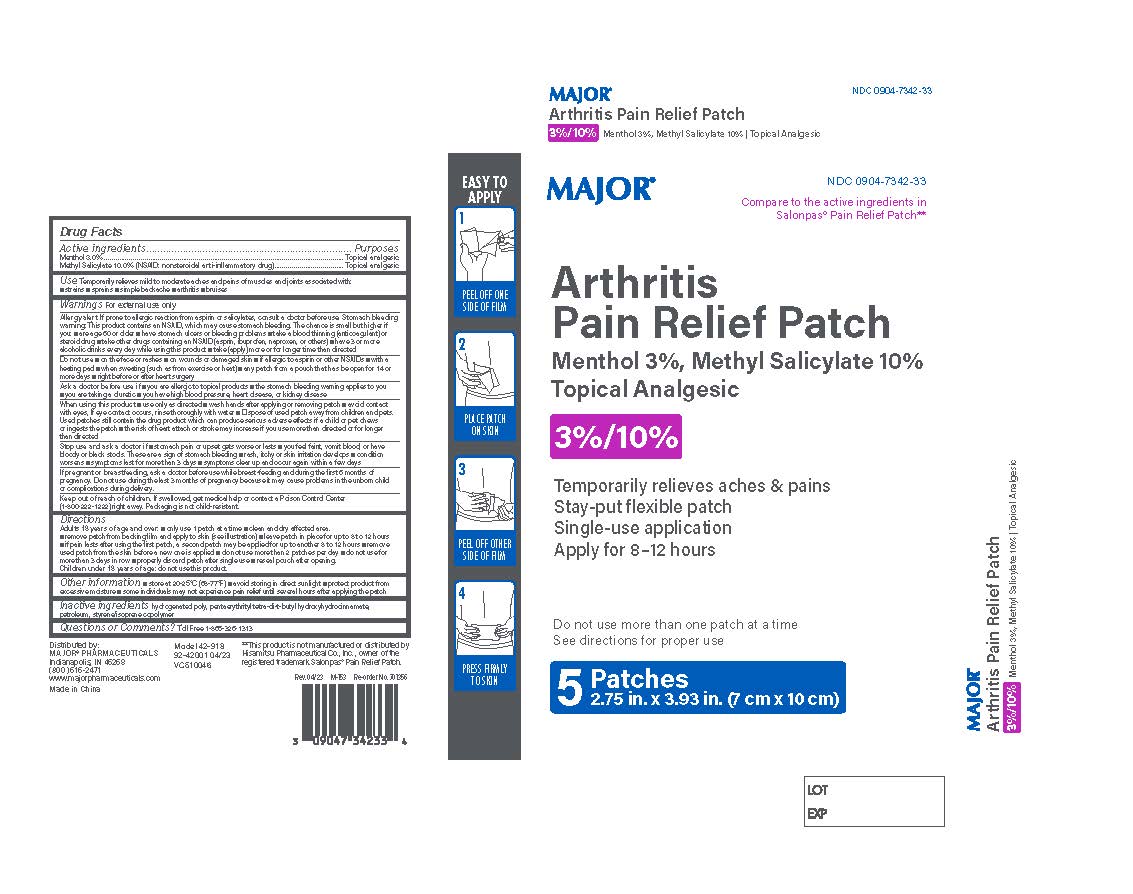 DRUG LABEL: Major Arthritis Pain Relief Patch
NDC: 0904-7342 | Form: PATCH
Manufacturer: Major Pharmaceuticals
Category: otc | Type: HUMAN OTC DRUG LABEL
Date: 20260218

ACTIVE INGREDIENTS: MENTHOL 3 g/100 g; METHYL SALICYLATE 10 g/100 g
INACTIVE INGREDIENTS: HYDROGENATED C6-20 POLYOLEFIN (100 CST); PENTAERYTHRITOL TETRAKIS(3-(3,5-DI-TERT-BUTYL-4-HYDROXYPHENYL)PROPIONATE); LIQUID PETROLEUM; STYRENE/ACRYLAMIDE COPOLYMER (MW 500000)

Major Arthritis Pain Relief Patch

Active Ingredients

Active Ingredients Purpose

Menthol 3.0% .......................Topical Analgesic

Methyl Salicylate 10.0% NSAID: nonsteroidal anti-inflammatory drug .......Topical Analgesic

For External Use Only

Allergy alert:If prone to allergic reaction from asprin or salicylates, consult a doctor before use Stomach bleeding
warning:This product contains an NSAID, which may cause stomach bleeding. The chance is small but higher if
you: ■ are age 60 or older ■ have stomach ulcers or bleeding problems ■ take a blood thinning (anticoagulant) or
steroid drug ■ take other drugs containing an NSAID (asprin, ibuprofen, naproxen, or others) ■ have 3 or more
alcoholic drinks every day while using this product ■ take (apply) more or for longer time than directed

Do not use:

on the face or rashes ■ on wounds or damaged skin ■ if allergic to aspirin or other NSAIDs ■ with a
heating pad ■ when sweating (such as from exercise or heat) ■ any patch from a pouch that has be open for 14 or
more days ■ right before or after heart surgery

When using this product

■ use only as directed ■ wash hands after applying or removing patch ■ avoid contact
with eyes, If eye contact occurs, rinse thoroughly with water ■ Dispose of used patch away from children and pets.
Used patches still contain the drug product which can produce serious adverse effects if a child or pet chews
or ingests the patch ■ the risk of heart attach or stroke may increase if you use more than directed or for longer
than directed

Stop use and consult a doctor

■ stomach pain or upset gets worse or lasts ■ you feel faint, vomit blood, or have
bloody or black stools. These are a sign of stomach bleeding ■ rash, itchy or skin irritation develops ■ condition
worsens ■ symptoms last for more than 3 days ■ symptoms clear up and occur again within a few days

Keep out of reach of children

If swallowed, get medical help or contact a Poison Control Center (1-800-222-1222) right away. Packaging is not child-resistant

Uses

For temporary relief of minor aches and pains of muscles and joints associated with arthritis, simple backache, strains, sprains, and bruises.

Directions

Adults 18 years of age and over: ■only use 1 patch at a time ■ clean and dry affected area.
■ remove patch from backing film and apply to skin (see illustration) ■ leave patch in place for up to 8 to 12 hours
■ if pain lasts after using the first patch, a second patch may be applied for up to another 8 to 12 hours ■ remove
used patch from the skin before a new one is applied ■ do not use more than 2 patches per day ■ do not use for
more than 3 days in row ■ properly discard patch after single use ■ reseal pouch after opening.
Children under 18 years of age:do not use this product.

Inactive Ingredients

Hydrogenated Poly, Pentaerythrityl Tetra-di-t-butyl Hydroxyhydrocinnamate, Petroleum, Styrene / Isoprene Copolymer

Indication and Usage

Temporarily relieves mild to moderate aches and pains of muscles and joints associated with:
■ strains ■ sprains ■ simple backache ■ arthritis ■ bruises

If pregnant or breastfeeding

ask a doctor before use while breast-feeding and during the first 6 months of
pregnancy. Do not use during the last 3 months of pregnancy because it may cause problems in the unborn child
or complications during delivery.

Ask a doctor before use

■ you are allergic to topical products ■ the stomach bleeding warning applies to you
■ you are taking a diuretic ■ you have high blood pressure, heart disease, or kidney disease

Questions or Comments?

Toll Free 1-866-326-1313

Other information

■ store at 20-25°C (68-77°F) ■ avoid storing in direct sunlight ■ protect product from
excessive moisture ■ some individuals may not experience pain relief until several hours after applying the patch